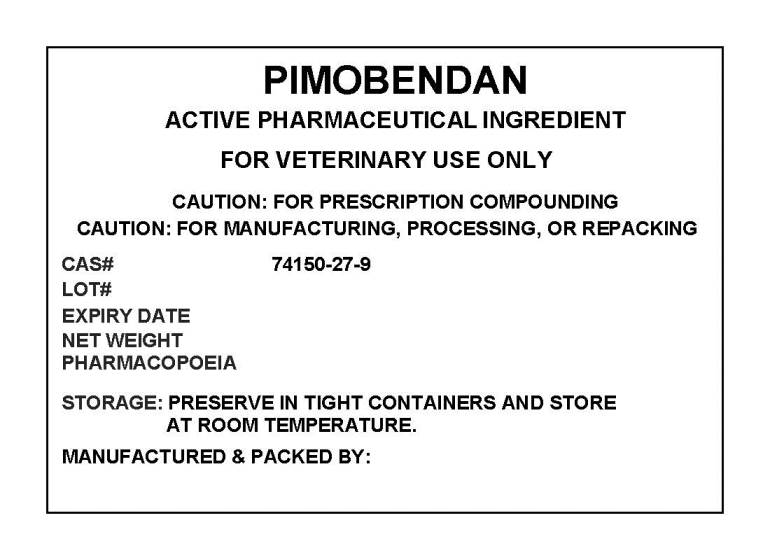 DRUG LABEL: PIMOBENDAN
NDC: 72969-059 | Form: POWDER
Manufacturer: PROFESSIONAL GROUP OF PHARMACISTS NEW YORK LLC
Category: other | Type: BULK INGREDIENT
Date: 20210311

ACTIVE INGREDIENTS: PIMOBENDAN 1 g/1 g

PIMOBENDAN

PACKAGE LABEL

pimobendanlabel.jpg